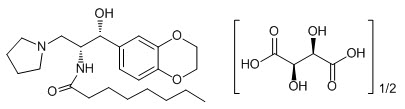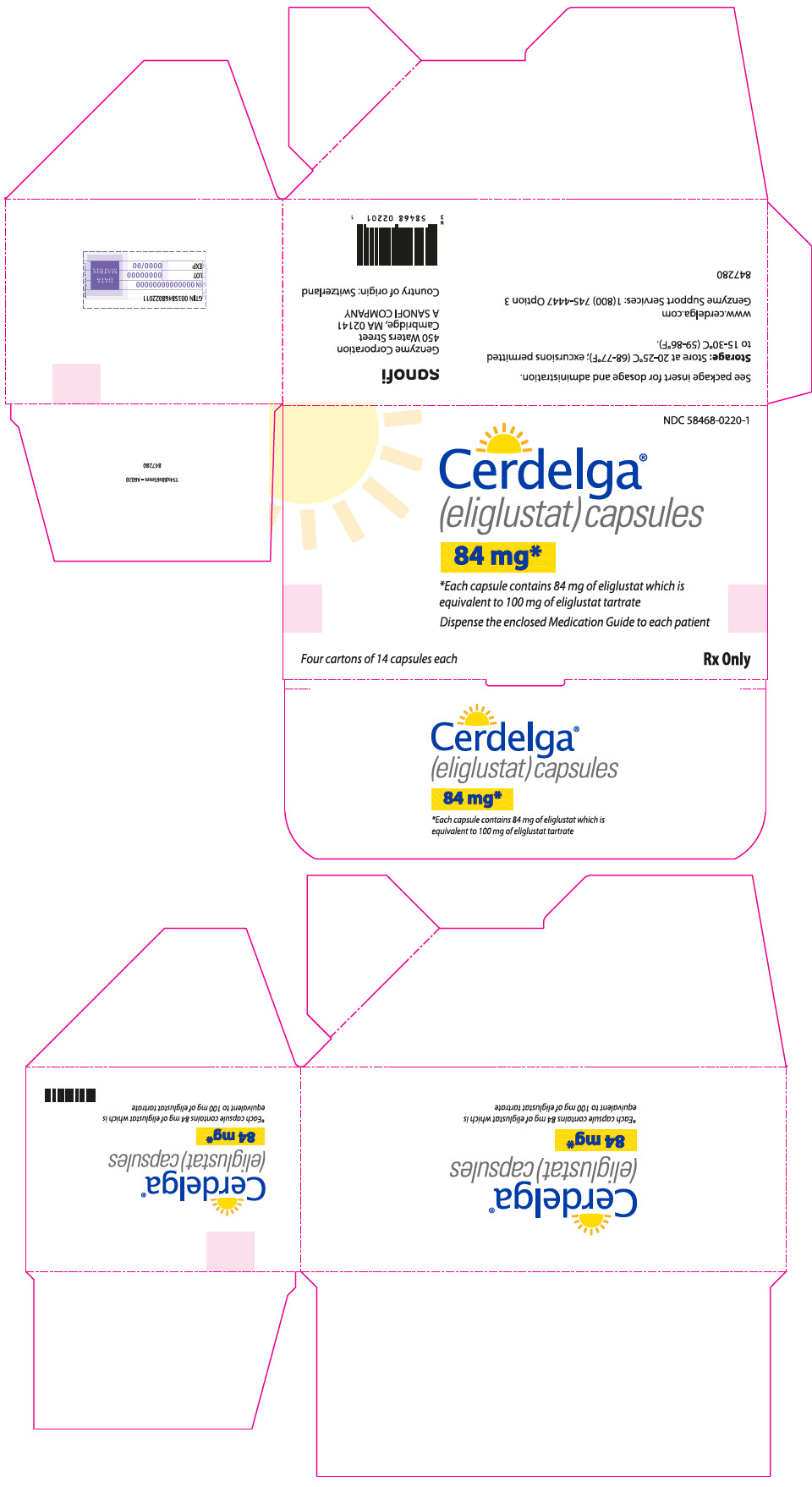 DRUG LABEL: Cerdelga
NDC: 58468-0220 | Form: CAPSULE
Manufacturer: Genzyme Corporation
Category: prescription | Type: HUMAN PRESCRIPTION DRUG LABEL
Date: 20240303

ACTIVE INGREDIENTS: ELIGLUSTAT 84 mg/1 1
INACTIVE INGREDIENTS: MICROCRYSTALLINE CELLULOSE; LACTOSE MONOHYDRATE; HYPROMELLOSE, UNSPECIFIED; GLYCERYL DIBEHENATE; GELATIN, UNSPECIFIED; MICA; TITANIUM DIOXIDE; FERRIC OXIDE YELLOW; FD&C BLUE NO. 2

HIGHLIGHTS OF PRESCRIBING INFORMATION

These highlights do not include all the information needed to use CERDELGA® safely and effectively. See full prescribing information for CERDELGA.
CERDELGA® (eliglustat) capsules, for oral use
Initial U.S. Approval: 2014

1 INDICATIONS AND USAGE

CERDELGA is a glucosylceramide synthase inhibitor indicated for the long-term treatment of adult patients with Gaucher disease type 1 who are CYP2D6 extensive metabolizers (EMs), intermediate metabolizers (IMs), or poor metabolizers (PMs) as detected by an FDA-cleared test. (1)

Limitations of Use:

- CYP2D6 ultra-rapid metabolizers may not achieve adequate concentrations of CERDELGA to achieve a therapeutic effect. (1)
- A specific dosage cannot be recommended for CYP2D6 indeterminate metabolizers. (1)

2 DOSAGE AND ADMINISTRATION

Patient Selection (2.1):

- Select patients using an FDA-cleared test for determining CYP2D6 genotype.

Recommended Dosage Based on CYP2D6 Metabolizer Status (2.2):

- EMs and IMs: 84 mg orally twice daily.
- PMs: 84 mg orally once daily.
- See the Full Prescribing Information for dosing recommendations in patients receiving CYP2D6 and/or CYP3A inhibitors, or with renal or hepatic impairment. (2.2, 4, 7.1, 8.6, 8.7)

Administration (2.4):

- Swallow capsules whole, do not crush, dissolve or open capsules. (2.4)
- Avoid eating grapefruit or drinking grapefruit juice. (2.4)

3 DOSAGE FORMS AND STRENGTHS

Capsules: 84 mg eliglustat

4 CONTRAINDICATIONS

EMs

- Taking a strong or moderate CYP2D6 inhibitor concomitantly with a strong or moderate CYP3A inhibitor. (4, 5.1, 7.1, 12.3)
- Moderate or severe hepatic impairment. (4, 5.1, 8.7, 12.3)
- Mild hepatic impairment taking a strong or moderate CYP2D6 inhibitor. (4, 5.1, 8.7, 12.3)

IMs

- Taking a strong or moderate CYP2D6 inhibitor concomitantly with a strong or moderate CYP3A inhibitor. (4, 5.1, 7.1, 12.3)
- Taking a strong CYP3A inhibitor. (4, 5.1, 7.1, 12.3)
- Any degree of hepatic impairment. (4, 5.1, 8.7, 12.3)

PMs

- Taking a strong CYP3A inhibitor (4, 5.1, 7.1, 12.3)
- Any degree of hepatic impairment (4, 5.1, 8.7, 12.3)

5 WARNINGS AND PRECAUTIONS

ECG Changes and Potential for Cardiac Arrhythmias: Not recommended in patients with pre-existing cardiac disease, long QT syndrome, and concomitant use of Class IA and Class III antiarrhythmics. (5.1)

6 ADVERSE REACTIONS

Most common adverse reactions (≥10%) are: fatigue, headache, nausea, diarrhea, back pain, pain in extremities, and upper abdominal pain. (6.1)

To report SUSPECTED ADVERSE REACTIONS, contact Genzyme Corporation at 1-800-745-4447 or FDA at 1-800-FDA-1088 or www.fda.gov/medwatch.

7 DRUG INTERACTIONS

See Full Prescribing Information for a list of clinically significant drug interactions. (7.1, 7.2)

FULL PRESCRIBING INFORMATION

1 INDICATIONS AND USAGE

CERDELGA is indicated for the long-term treatment of adult patients with Gaucher disease type 1 (GD1) who are CYP2D6 extensive metabolizers (EMs), intermediate metabolizers (IMs), or poor metabolizers (PMs) as detected by an FDA-cleared test [see Dosage and Administration (2.1)].

Limitations of Use:

- Patients who are CYP2D6 ultra-rapid metabolizers (URMs) may not achieve adequate concentrations of CERDELGA to achieve a therapeutic effect [see Clinical Studies (14)].
- A specific dosage cannot be recommended for those patients whose CYP2D6 genotype cannot be determined (indeterminate metabolizers) [see Clinical Studies (14)].

2 DOSAGE AND ADMINISTRATION

2.1 Patient Selection

Select patients with Gaucher disease type 1 based on their CYP2D6 metabolizer status. It is recommended patient genotypes be established using an FDA-cleared test for determining CYP2D6 genotype [see Indications and Usage (1)].

2.2 Recommended Adult Dosage

The recommended dosage of CERDELGA in adults is based on the patient's CYP2D6 metabolizer status.

Table 1: Recommended Dosage Regimen by CYP2D6 Metabolizer Status
CYP2D6 Metabolizer Status | CERDELGA Dosage
EMs | 84 mg twice daily
IMs | 84 mg twice daily
PMs | 84 mg once daily

2.3 Dosage Adjustment in EMs and IMs With or Without Hepatic Impairment and Concomitant Use of CYP2D6 or CYP3A Inhibitors

Reduce dosage frequency of CERDELGA 84 mg to once daily in CYP2D6 EMs and IMs with or without hepatic impairment taking CYP2D6 or CYP3A inhibitors, as shown in Table 2 [see Warnings and Precautions (5.1), Drug Interactions (7.1), Use in Specific Populations (8.7)].

Table 2: Recommended Dosage of CERDELGA 84 mg Once Daily based on CYP2D6 Metabolizer, Hepatic Impairment Status, and Concomitant CYP Inhibitors
CYP2D6 Metabolizer Status | Hepatic Impairment Status | Concomitant CYP Inhibitor
EMs | Without Hepatic Impairment | - Taking a strong or moderate CYP2D6 inhibitor - Taking a strong or moderate CYP3A inhibitor
EMs | Mild (Child-Pugh Class A) Hepatic Impairment | - Taking a weak CYP2D6 inhibitor - Taking a strong, moderate, or weak CYP3A inhibitor
IMs | Without Hepatic Impairment | - Taking a strong or moderate CYP2D6 inhibitor

2.4 Important Administration Instructions

- Swallow capsules whole, preferably with water, and do not crush, dissolve, or open the capsules.
- CERDELGA can be taken with or without food.
- Avoid the consumption of grapefruit or grapefruit juice (strong CYP3A inhibitors) with CERDELGA [see Drug Interactions (7.1)].
- If a dose of CERDELGA is missed, take the prescribed dose at the next scheduled time; do not double the next dose.
- For patients currently treated with imiglucerase, velaglucerase alfa, or taliglucerase alfa, CERDELGA may be administered 24 hours after the last dose of the previous enzyme replacement therapy (ERT).

3 DOSAGE FORMS AND STRENGTHS

Capsules: 84 mg of eliglustat is in a capsule with a pearl blue-green opaque cap and pearl white opaque body imprinted with "GZ02" in black.

4 CONTRAINDICATIONS

CERDELGA is contraindicated in the following patients based on CYP2D6 metabolizer status due to the risk of cardiac arrhythmias from prolongation of the PR, QTc, and/or QRS cardiac intervals.

EMs

- Taking a strong or moderate CYP2D6 inhibitor concomitantly with a strong or moderate CYP3A inhibitor [see Drug Interactions (7.1)]
- Moderate or severe hepatic impairment [see Use in Specific Populations (8.7)]
- Mild hepatic impairment and taking a strong or moderate CYP2D6 inhibitor [see Use in Specific Populations (8.7)]

IMs

- Taking a strong or moderate CYP2D6 inhibitor concomitantly with a strong or moderate CYP3A inhibitor [see Drug Interactions (7.1)]
- Taking a strong CYP3A inhibitor [see Drug Interactions (7.1)]
- Any degree of hepatic impairment [see Use in Specific Populations (8.7)]

PMs

- Taking a strong CYP3A inhibitor [see Drug Interactions (7.1)]
- Any degree of hepatic impairment [see Use in Specific Populations (8.7)]

5 WARNINGS AND PRECAUTIONS

5.1 ECG Changes and Potential for Cardiac Arrhythmias

CERDELGA is predicted to cause increases in ECG intervals (PR, QTc, and QRS) at substantially elevated eliglustat plasma concentrations and may increase the risk of cardiac arrhythmias.

- Use of CERDELGA is contraindicated, to be avoided, or requires dosage adjustment in patients taking CYP2D6 or CYP3A inhibitors, depending on CYP2D6 metabolizer status, type of inhibitor, or degree of hepatic impairment [see Dosage and Administration (2.3), Contraindications (4), Drug Interactions (7.1)].

Use of CERDELGA in patients with pre-existing cardiac conditions has not been studied during clinical trials. Avoid use of CERDELGA in patients with:

- pre-existing cardiac disease (congestive heart failure, recent acute myocardial infarction, bradycardia, heart block, ventricular arrhythmia)
- long QT syndrome
- in combination with Class IA (e.g., quinidine, procainamide) or Class III (e.g., amiodarone, sotalol) antiarrhythmic medications [see Clinical Pharmacology (12.2)]

6 ADVERSE REACTIONS

6.1 Clinical Trials Experience

Because clinical trials are conducted under widely varying conditions, adverse reaction rates observed in the clinical trials of a drug cannot be directly compared to rates in the clinical trials of another drug and may not reflect the rates observed in practice.

The most common adverse reactions to CERDELGA (occurring in ≥10% of the 126 GD1 patients treated with CERDELGA across Trials 1 and 2) were fatigue, headache, nausea, diarrhea, back pain, pain in extremities, and upper abdominal pain.

The adverse reaction profile of CERDELGA is based on two controlled studies, Trials 1 and 2 [see Clinical Studies (14.1, 14.2)]. Table 3 presents the profile from the 9-month double-blind, randomized, placebo-controlled trial of 40 treatment-naive patients (Trial 1). Patients were between the ages of 16 and 63 on the date of the first dose of study drug, and included 20 males and 20 females.

Table 3: Adverse Reactions Occurring in ≥10% of Treatment-Naive GD1 Patients and More Frequently than Placebo (Trial 1)
 | CERDELGA (N=20) | Placebo (N=20)
Adverse Reaction | Patients n (%) | Patients n (%)
Arthralgia | 9 (45) | 2 (10)
Headache | 8 (40) | 6 (30)
Migraine | 2 (10) | 0 (0)
Flatulence | 2 (10) | 1 (5)
Nausea | 2 (10) | 1 (5)
Oropharyngeal pain | 2 (10) | 1 (5)

Table 4 presents the profile from the 12-month open-label, randomized, imiglucerase-controlled trial of 159 treated patients switching from enzyme replacement therapy (ERT) (Trial 2). Patients were between the ages of 18 and 69 on the date of the first dose of CERDELGA, and included 87 females and 72 males.

Table 4: Adverse Reactions Occurring in ≥5% of GD1 Patients Switching from Enzyme Replacement Therapy to CERDELGA and More Frequently than Imiglucerase (Trial 2) [Trial 2 was not designed to support comparative claims for CERDELGA for the adverse reactions reported in this table.]
 | CERDELGA (N=106) | Imiglucerase (N=53)
Adverse Reaction | Patients n (%) | Patients n (%)
Fatigue | 15 (14) | 1 (2)
Headache | 14 (13) | 1 (2)
Nausea | 13 (12) | 0 (0)
Diarrhea | 13 (12) | 2 (4)
Back pain | 13 (12) | 3 (6)
Pain in extremity | 12 (11) | 1 (2)
Upper abdominal pain | 11 (10) | 0 (0)
Dizziness | 9 (8) | 0 (0)
Asthenia | 9 (8) | 0 (0)
Cough | 7 (7) | 2 (4)
Dyspepsia | 7 (7) | 1 (2)
Gastroesophageal reflux disease | 7 (7) | 0 (0)
Constipation | 5 (5) | 0 (0)
Palpitations | 5 (5) | 0 (0)
Rash | 5 (5) | 0 (0)

In a separate uncontrolled study, with up to 4 years of treatment in 26 naive GD1 patients, the types and incidences of adverse reactions were similar to Trials 1 and 2.

7 DRUG INTERACTIONS

7.1 Effect of Other Drugs on CERDELGA

Coadministration of CERDELGA with:

- CYP2D6 or CYP3A inhibitors may increase eliglustat concentrations which may increase the risk of cardiac arrhythmias from prolongation of the PR, QTc, and/or QRS cardiac interval [see Warnings and Precautions (5.1), Clinical Pharmacology (12.3)].
- strong CYP3A inducers decrease eliglustat concentrations which may reduce CERDELGA efficacy [see Clinical Pharmacology (12.3)].

See Table 5 for prevention and management of interactions with drugs affecting CERDELGA. Use of CERDELGA is contraindicated, to be avoided, or may require dosage adjustment depending on the concomitant drug and CYP2D6 metabolizer status [see Dosage and Administration (2.2, 2.3), Contraindications (4), Drug Interactions (7.1)].

Table 5: Prevention and Management Strategies of Drug Interactions Affecting CERDELGA Based on CYP2D6 Metabolizer Status and Concomitant Interacting Drug
Concomitant Drug(s) | CYP2D6 Metabolizer Status
Concomitant Drug(s) | EMs | IMs | PMs
CYP2D6 Inhibitor
Strong | Reduce frequency of CERDELGA 84 mg to once daily |  | Continue CERDELGA 84 mg once daily [No effect of CYP2D6 inhibitor due to little or no CYP2D6 activity in CYP2D6 PMs.]
Moderate | Reduce frequency of CERDELGA 84 mg to once daily |  | Continue CERDELGA 84 mg once daily [No effect of CYP2D6 inhibitor due to little or no CYP2D6 activity in CYP2D6 PMs.]
Weak | Continue CERDELGA 84 mg twice daily |  | Continue CERDELGA 84 mg once daily [No effect of CYP2D6 inhibitor due to little or no CYP2D6 activity in CYP2D6 PMs.]
CYP3A Inhibitor
Strong | Reduce frequency of CERDELGA 84 mg to once daily | Contraindicated
Moderate | Reduce frequency of CERDELGA 84 mg to once daily | Avoid coadministration
Weak | Continue CERDELGA 84 mg twice daily |  | Avoid coadministration
CYP2D6 Inhibitor Concomitantly with a strong CYP3A Inhibitor
Strong | Contraindicated
Moderate | Contraindicated
CYP2D6 Inhibitor Concomitantly with a moderate CYP3A Inhibitor
Strong | Contraindicated |  | Avoid coadministration
Moderate | Contraindicated |  | Avoid coadministration
CYP3A Inducer
Strong | Avoid coadministration

7.2 Effect of CERDELGA on Other Drugs

See Table 6 for clinically relevant interactions affecting P-gp or CYP2D6 substrates when coadministered with CERDELGA.

Table 6: Prevention and Management Strategies of Drug Interactions Affecting Other Drugs
Substrates for P-gp or CYP2D6
Clinical Impact | Coadministration of CERDELGA may increase concentrations of drugs that are substrates for P-gp or CYP2D6 [see Clinical Pharmacology (12.3)] and may increase the risk of toxicity of these drugs.
Prevention or Management | Digoxin | Monitor serum digoxin concentrations before initiating CERDELGA. Reduce digoxin dose by 30% and continue monitoring.
Prevention or Management | Other P-gp substrates or CYP2D6 substrates | Monitor therapeutic drug concentrations, as indicated, or consider reducing the dosage of the concomitant drug and titrate to clinical effect.

8 USE IN SPECIFIC POPULATIONS

8.1 Pregnancy

Risk Summary

Available data on CERDELGA use in pregnant women includes 20 pregnancies that occurred during the clinical development program and a small number of post-marketing case reports. These data are not sufficient to assess drug-associated risks major birth defects, miscarriage, or adverse maternal or fetal outcomes. In animal reproduction studies in pregnant rats administered oral eliglustat during organogenesis, a spectrum of various developmental abnormalities were observed at doses 6 times the recommended human dose. No adverse developmental outcomes were observed with oral administration of eliglustat to pregnant rabbits at dose levels 10 times the recommended human dose [see Data].

The estimated background risk of major birth defects and miscarriage in the indicated population is unknown. All pregnancies have a background risk of birth defect, loss or other adverse outcomes. In the U.S. general population, the estimated background risk of major birth defects and miscarriage in clinically recognized pregnancies is 2% to 4% and 15% to 20%, respectively.

Clinical Considerations

Disease-associated maternal and/or embryo/fetal risk

Women with Gaucher disease type 1 have an increased risk of spontaneous abortion, especially if disease symptoms are not treated and controlled pre-conception and during a pregnancy. Pregnancy may exacerbate existing Gaucher disease type 1 symptoms or result in new disease manifestations. Gaucher disease type 1 manifestations may lead to adverse pregnancy outcomes including, hepatosplenomegaly which can interfere with the normal growth of a pregnancy and thrombocytopenia which can lead to increased bleeding and possible hemorrhage.

Data

Animal data

Reproduction studies have been performed in pregnant rats at oral doses up to 120 mg/kg/day (about 6 times the recommended human dose based on body surface area) and in pregnant rabbits at oral doses up to 100 mg/kg/day (about 10 times the recommended human dose based on body surface area) following administration of eliglustat during the period of organogenesis (gestation days 6 to 17 in the rat and 6 to 18 in the rabbit).

In rats, at 120 mg/kg/day (about 6 times the recommended human dose based on body surface area), eliglustat increased the number of late resorptions, dead fetuses and post implantation loss, reduced fetal body weight, and caused fetal cerebral variations (dilated cerebral ventricles), fetal skeletal variations (poor bone ossification) and fetal skeletal malformations (abnormal number of ribs or lumbar vertebra). Eliglustat-related effects on fetal rats were observed in association with signs of maternal toxicity.

Eliglustat did not cause fetal harm in rabbits at oral doses up to 100 mg/kg/day (about 10 times the recommended human dose based on body surface area). Mild maternal toxicity was observed at the 100 mg/kg/day dose.

In a pre and postnatal development study in rats (dosed daily from gestation day 6 to postpartum day 21), eliglustat did not show any significant adverse effects on pre and postnatal development at doses up to 100 mg/kg/day (about 5 times the recommended human dose based on body surface area).

8.2 Lactation

Risk Summary

There are no human data available on the presence of eliglustat in human milk, the effects on the breastfed infant, or the effects on milk production. Eliglustat and its metabolites were present in the milk of lactating rats [see Data]. When a drug is present in animal milk, it is likely that the drug will be present in human milk. The developmental and health benefits of breastfeeding should be considered along with the mother's clinical need for CERDELGA and any potential adverse effects on the breastfed child from CERDELGA or from the underlying maternal condition.

Data

In a milk excretion study in the rat, a single oral dose of 30 mg/kg [^14C]-labeled eliglustat was administered to lactating female rats at day 11 postpartum. Approximately 0.23% of the administered radioactivity was excreted into the milk within 24 hours of dose administration. The concentration in the milk at 24 hours post dose was 16.3-fold higher than the plasma concentration.

8.4 Pediatric Use

Safety and effectiveness in pediatric patients have not been established.

8.5 Geriatric Use

Clinical studies of CERDELGA did not include sufficient numbers of subjects aged 65 and over to determine whether they respond differently from younger subjects. Clinical experience has not identified differences in responses between the elderly and younger patients.

8.6 Renal Impairment

Use CERDELGA in patients with renal impairment based on the patient's CYP2D6 metabolizer status [see Clinical Pharmacology (12.3)].

EMs

- Avoid CERDELGA in patients with end-stage renal disease (ESRD) (estimated creatinine clearance (eCLcr) less than 15 mL/min not on dialysis or requiring dialysis).
- No dosage adjustment is recommended in patients with mild, moderate, or severe renal impairment (eCLcr at least 15 mL/min).

IMs and PMs

- Avoid CERDELGA in patients with any degree of renal impairment.

8.7 Hepatic Impairment

Use CERDELGA in patients with hepatic impairment based on CYP2D6 metabolizer status and concomitant use of CYP2D6 or CYP3A inhibitors [see Clinical Pharmacology (12.3)].

EMs

- CERDELGA is contraindicated in patients with [see Contraindications (4)]:
  - severe (Child-Pugh Class C) hepatic impairment
  - moderate (Child-Pugh Class B) hepatic impairment
  - mild (Child-Pugh Class A) hepatic impairment taking a strong or moderate CYP2D6 inhibitor
- Reduce dosage frequency of CERDELGA 84 mg to once daily [see Dosage and Administration (2.3)] in patients with mild hepatic impairment taking:
  - a weak CYP2D6 inhibitor
  - a strong, moderate, or weak CYP3A inhibitor
- No dosage adjustment is recommended in patients with mild hepatic impairment, unless otherwise specified above.

IMs and PMs

- CERDELGA is contraindicated in patients with any degree of hepatic impairment [see Contraindications (4)].

10 OVERDOSAGE

The highest eliglustat plasma concentration experienced to date occurred in a single-dose, dose escalation study in healthy subjects, in a subject taking a dose equivalent to approximately 21 times the recommended dose for GD1 patients. At the time of the highest plasma concentration (59-fold higher than normal therapeutic conditions), the subject experienced dizziness marked by disequilibrium, hypotension, bradycardia, nausea, and vomiting.

In the event of acute overdose, the patient should be carefully observed and given symptomatic and supportive treatment.

Hemodialysis is unlikely to be beneficial given that eliglustat has a large volume of distribution [see Clinical Pharmacology (12.3)].

11 DESCRIPTION

CERDELGA (eliglustat) capsules contain eliglustat tartrate, which is a small molecule inhibitor of glucosylceramide synthase that resembles the ceramide substrate for the enzyme, with the chemical name N-((1R,2R)-1-(2,3-dihydrobenzo[b][1,4]dioxin-6-yl)-1-hydroxy-3-(pyrrolidin-1-yl)propan-2-yl)octanamide (2R,3R)-2,3-dihydroxysuccinate. Its molecular weight is 479.59, and the empirical formula is C23H36N2O4+½(C4H6O6) with the following chemical structure:

Each capsule of CERDELGA for oral use contains 84 mg of eliglustat (equivalent to 100 mg of eliglustat tartrate). The inactive ingredients are candurin silver fine, FD&C blue 2, gelatin, glyceryl behenate, hypromellose, lactose monohydrate, microcrystalline cellulose, and yellow iron oxide.

12 CLINICAL PHARMACOLOGY

12.1 Mechanism of Action

Gaucher disease is caused by a deficiency of the lysosomal enzyme acid β-glucosidase. Acid β-glucosidase catalyzes the conversion of the sphingolipid glucocerebroside into glucose and ceramide. The enzymatic deficiency causes an accumulation of glucosylceramide (GL-1) primarily in the lysosomal compartment of macrophages, giving rise to foam cells or "Gaucher cells."

The clinical features of this lysosomal storage disorder (LSD) are reflective of the accumulation of Gaucher cells in the reticuloendothelial system (liver, spleen, bone marrow, and other organs). The accumulation of Gaucher cells in the liver, spleen, and bone marrow leads to organomegaly and skeletal disease. Presence of Gaucher cells in the bone marrow and spleen leads to clinically significant anemia and thrombocytopenia.

CERDELGA is a specific inhibitor of glucosylceramide synthase (IC50=10 ng/mL) and acts as a substrate reduction therapy for GD1 by reducing the production of GL-1. By reducing GL-1 production, CERDELGA alleviates the accumulation of GL-1 in the target organs.

12.2 Pharmacodynamics

Effects on spleen and liver volume, hemoglobin, and platelets increased with increasing steady-state average trough concentrations of eliglustat ranging up to 14 ng/mL in treatment naive patients in Trial 1. In patients previously treated with enzyme-replacement therapy in Trial 2 [see Clinical Studies (14.2)], no clinically relevant exposure-response relationship was observed.

Cardiac Electrophysiology

Concentration-related increases were observed for the placebo-corrected change from baseline in the PR, QRS, and QTc intervals. At the mean peak concentration of 237 ng/mL at a dose of 800 mg eliglustat tartrate (8 times the recommended dose), CERDELGA did not prolong the QT/QTc interval to any clinically relevant extent. However, pharmacokinetic/pharmacodynamic modeling predicts mean (upper bound of the 95% one-sided confidence interval) increases in the PR, QRS, and QTcF intervals of 22 (26), 7 (10), and 13 (19) msec, respectively, at eliglustat plasma concentration of 500 ng/mL [see Warnings and Precautions (5.1)].

12.3 Pharmacokinetics

Absorption

The oral bioavailability of eliglustat was less than 5% in CYP2D6 EMs following a single 84 mg dose of CERDELGA.

In CYP2D6 EMs, the eliglustat pharmacokinetics is time-dependent and the systemic exposure increases in a more than dose-proportional manner over the dose range of 42 to 294 mg (0.5 to 3.5 times the recommended dosage). In addition, after multiple oral doses of 84 mg twice daily in EMs, eliglustat systemic exposure (AUC0–12) increased up to about 2-fold at steady state compared to after the first dose (AUC0–∞). The pharmacokinetics of eliglustat in CYP2D6 PMs is expected to be linear and time-independent. Compared to EMs, the systemic exposure following 84 mg twice daily at steady state is 7-fold to 9-fold higher in PMs.

Dosing of CERDELGA 84 mg once daily has not been studied in PMs. The predicted Cmax and AUC0–24hr in PMs using a physiologically based pharmacokinetic (PBPK) model with 84 mg once daily were 75 ng/mL and 956 hr∙ng/mL, respectively.

Table 7 describes the pharmacokinetic parameters for eliglustat in healthy subjects following multiple doses of 84 mg CERDELGA twice daily.

Table 7: Pharmacokinetic Parameters for Eliglustat following Multiple Doses of 84 mg CERDELGA Twice Daily
Parameter | CYP2D6 Metabolizer Status
Parameter | EMs (n=96) | IMs (n=1) | PMs [84 mg twice daily is not the recommended dosage in PMs [see Dosage and Administration (2.2)].] (n=9)
Cmax (ng/mL) [Range of the mean (CV%) values from multiple studies.] | 12.1 (42%) to 25.0 (141%) | 44.6 | 113 (32%) to 137 (40%)
AUCtau (ng∙hr/mL) | 76.3 (37%) to 143 (160%) | 306 | 922 (33%) to 1057 (38%)
Median Tmax (hr) [min to max] [Range of the median time to reach maximum plasma concentration (Tmax) from multiple studies.] | 1.5 [0.5 to 3.0] to 2 [1.5 to 2.1] | 2 | 3 [2 to 4]

Administration of CERDELGA with a high fat meal (approximately 1000 calories with 50% calories from fat) resulted in a 15% decrease in Cmax (not clinically significant) but no change in AUC.

Distribution

Following intravenous administration, the volume of distribution of eliglustat was 835 L in EMs. Plasma protein binding of eliglustat ranges from 76% to 83%.

Elimination

Eliglustat terminal elimination half-life was approximately 6.5 hours in CYP2D6 EMs, and 8.9 hours in PMs. Following intravenous administration of 42 mg (0.5 times the recommended oral dose) in healthy subjects, the mean (range) of eliglustat total body clearance was 88 L/h (80 to 105 L/h) in EMs.

Metabolism

CERDELGA is primarily metabolized by CYP2D6 and to a lesser extent by CYP3A4.

Excretion

After oral administration of radiolabeled eliglustat, the majority of the administered dose is excreted in urine (42%) and feces (51%), mainly as metabolites.

Specific Populations

No clinically significant differences in the pharmacokinetics of eliglustat were observed based on age (18 to 71 years), sex, race (mostly were Caucasian, including those of Ashkenazi Jewish descent; however, it included the following populations: African American, American Indians, Hispanics, and Asians), or body weight (41 to 136 kg).

Patients with renal impairment

Eliglustat pharmacokinetics was similar in CYP2D6 EMs with severe renal impairment and healthy CYP2D6 EMs. Eliglustat pharmacokinetics in EMs with ESRD and in IMs or PMs with any degree of renal impairment is unknown [see Use in Specific Populations (8.6)].

Patients with hepatic impairment

Table 8 describes the effect of mild and moderate hepatic impairment on the pharmacokinetics of eliglustat in CYP2D6 EMs compared to EMs with normal hepatic function following a single 84 mg dose. The effect of hepatic impairment is highly variable with the coefficients of variation (CVs%) of 135% and 110% for Cmax and 171% and 121% for AUC in CYP2D6 EMs with mild and moderate hepatic impairment, respectively.

Table 8: Effect of Hepatic Impairment on Eliglustat Pharmacokinetics following a Single Dose of 84 mg CERDELGA in CYP2D6 EMs
 | Mild Hepatic Impairment (n=6) | Moderate Hepatic Impairment (n=7)
Cmax | ↑ 1.2-fold | ↑ 2.8-fold
AUC | ↑ 1.2-fold | ↑ 5.2-fold

Steady-state pharmacokinetics of eliglustat in CYP2D6 IMs and PMs with mild and moderate hepatic impairment is unknown. The effect of severe hepatic impairment in subjects with any CYP2D6 phenotype is unknown [see Use in Specific Populations (8.7)].

Drug Interaction Studies

Effect of other drugs on CERDELGA

Table 9 describes the effect of drug interactions on the pharmacokinetics of eliglustat [see Drug Interactions (7.1)].

Table 9: Drug Interactions Affecting Eliglustat Concentrations
Concomitant Drug(s) | CYP2D6 Metabolizer Status
Concomitant Drug(s) | EMs |  | IMs |  | PMs
Concomitant Drug(s) | Cmax | AUCtau | Cmax | AUCtau | Cmax | AUCtau
CYP2D6 Inhibitor
Paroxetine (strong) | ↑ 7.0-fold | ↑ 8.4-fold | ↑ 2.1-fold [Predicted pharmacokinetic parameters based on PBPK models.] | ↑ 2.3-fold | No increase expected [Due to little or no CYP2D6 activity in CYP2D6 PMs.]
Terbinafine (moderate) | ↑ 3.8-fold | ↑ 4.5-fold | ↑ 1.6-fold |  | No increase expected [Due to little or no CYP2D6 activity in CYP2D6 PMs.]
CYP3A Inhibitor
Ketoconazole (strong) | ↑ 4.0-fold | ↑ 4.4-fold | ↑ 4.4-fold | ↑ 5.4-fold | ↑ 4.3- fold, [Following coadministration with CERDELGA 84 mg once daily.] | ↑ 6.2- fold,
Fluconazole (moderate) | ↑ 2.8-fold | ↑ 3.2-fold | ↑ 2.5-fold | ↑ 2.9-fold | ↑ 2.4- fold, | ↑ 3.0- fold,
CYP2D6 Inhibitors Concomitantly with CYP3A Inhibitors
Paroxetine with ketoconazole | ↑ 16.7-fold | ↑ 24.2-fold | ↑ 7.5-fold | ↑ 9.8-fold | Expected similar increase as with CYP3A inhibitors alone
Terbinafine with fluconazole | ↑ 10.2-fold | ↑ 13.6-fold | ↑ 4.2-fold | ↑ 5.0-fold | Expected similar increase as with CYP3A inhibitors alone
CYP3A Inducers
Rifampin (strong) | ↓ 90% [Following coadministration with CERDELGA 127 mg twice daily (1.5 times the recommended dosage).] |  |  |  | ↓ 95%
↑ = Increased; ↓ = Decreased

No clinically significant pharmacokinetic changes were observed for eliglustat when coadministered with intravenous rifampin (an OATP inhibitor), or gastric pH modifying drugs (e.g., aluminum hydroxide, magnesium hydroxide, calcium carbonate, pantoprazole).

In vitro, eliglustat is a substrate of P-glycoprotein (P-gp). The effect of P-gp inhibitors on eliglustat pharmacokinetics is unknown.

Effect of CERDELGA on other drugs

CYP2D6 substrates

Following multiple doses of CERDELGA 127 mg twice daily (1.5 times the recommended dosage), metoprolol (a CYP2D6 substrate) mean Cmax and AUC increased by 1.7-fold and 2.3-fold in CYP2D6 EMs, respectively, and by 1.2-fold and 1.6-fold in IMs, respectively [see Drug Interactions (7.2)].

P-gp substrates

Following multiple doses of CERDELGA 127 mg twice daily (1.5 times the recommended dosage) in CYP2D6 EMs and IMs, or 84 mg twice daily in PMs, digoxin (a P-gp substrate) mean Cmax increased by 1.7-fold and AUC increased by 1.5-fold [see Drug Interactions (7.2)].

Oral contraceptives

Repeated doses of CERDELGA 84 mg twice daily did not change the exposures to norethindrone (1.0 mg) and ethinyl estradiol (0.035 mg).

13 NONCLINICAL TOXICOLOGY

13.1 Carcinogenesis, Mutagenesis, Impairment of Fertility

Carcinogenesis

Carcinogenic potential of CERDELGA was assessed in 2-year carcinogenicity studies in rats and mice. In Sprague-Dawley rats, eliglustat was administered by oral gavage at doses up to 75 mg/kg/day in males (about 3.6 times the recommended human daily dose of 84 mg twice daily, based on body surface area) and 50 mg/kg/day in females (about 2.4 times the recommended human daily dose based on body surface area). In CD-1 mice, eliglustat was administered to males and females at up to 75 mg/kg/day (about 1.8 times the recommended human daily dose based on body surface area) via dietary admixture. Eliglustat did not produce any treatment-related neoplasms in rats or mice.

Mutagenesis

Eliglustat was negative in the Ames test, chromosome aberration test in human peripheral blood lymphocytes, mouse lymphoma gene mutation assay and in vivo oral mouse micronucleus test.

Impairment of Fertility

In a fertility and early embryonic development study in rats, eliglustat increased pre-implantation loss at 30 (about 1.5 times the recommended human oral dose based on body surface area) and 100 mg/kg/day (about 5 times the recommended human oral dose based on body surface area).

In mature male rats, eliglustat showed reversible adverse effects on sperm morphology, testes (germ cell necrosis), and sloughed cells in the epididymis at 200 mg/kg/day (about 10 times the recommended human oral dose based on body surface area). Similar effects on sperm were not seen in mature cynomolgus monkeys at 72 mg/kg/day (about 7 times the recommended human oral dose based on body surface area).

14 CLINICAL STUDIES

14.1 CERDELGA in Treatment-Naive GD1 Patients – Trial 1

Trial 1 (NCT00891202) was a randomized, double-blind, placebo-controlled, multicenter clinical study evaluating the efficacy and safety of CERDELGA in 40 treatment- naive GD1 patients 16 years of age or older (median age 30.4 years) with pre-existing splenomegaly and hematological abnormalities. Patients were required to have received no treatment with substrate reduction therapy within 6 months or ERT within 9 months prior to randomization; all but 5 patients in the study had no prior therapy. Patients were stratified according to baseline spleen volume (≤20 or >20 multiples of normal [MN]) and randomized in a 1:1 ratio to receive CERDELGA or placebo for the duration of the 9-month blinded primary analysis period. The CERDELGA treatment group was comprised of IM (5%), EM (90%) and URM (5%) patients. Patients randomized to CERDELGA treatment received a starting dose of 42 mg twice daily, with a dose increase to 84 mg twice daily possible at Week 4 based on the plasma trough concentration at Week 2. The majority of patients (17 [85%]) received a dose escalation to 84 mg twice daily at Week 4, and 3 (15%) continued to receive 42 mg twice daily for the duration of the 9-month blinded primary analysis period.

The primary endpoint was the percentage change in spleen volume (in MN) from baseline to 9 months as compared to placebo. Secondary endpoints were absolute change in hemoglobin level, percentage change in liver volume (in MN), and percentage change in platelet count from baseline to 9 months compared to placebo.

At baseline, mean spleen volumes were 12.5 and 13.9 MN in the placebo and CERDELGA groups, respectively, and mean liver volumes were 1.4 MN for both groups. Mean hemoglobin levels were 12.8 and 12.1 g/dL, and platelet counts were 78.5 and 75.1 × 10^9/L, respectively.

During the 9-month primary analysis period, CERDELGA demonstrated statistically significant improvements in all primary and secondary endpoints compared to placebo, as shown in Table 10.

Table 10: Change from Baseline to Month 9 in Treatment-Naive Patients with GD1 Receiving Treatment with CERDELGA in Trial 1
 | Placebo (n=20) | CERDELGA (n=20) | Difference (CERDELGA – Placebo) [95% CI] | p value [Estimates and p-value are based on ANCOVA model that includes treatment group, baseline spleen severity group (≤20 MN, >20 MN) and baseline parameter value.]
Percentage Change in Spleen Volume MN (%) | 2.3 | -27.8 | -30.0 [-36.8, -23.2] | <0.0001
Absolute Change in Spleen Volume (MN) | 0.3 | -3.7 | -4.1 [-5.3, -2.9] | NA
Absolute Change in Hemoglobin Level (g/dL) | -0.5 | 0.7 | 1.2 [0.6, 1.9] | 0.0006
Percentage Change in Liver Volume MN (%) | 1.4 | -5.2 | -6.6 [-11.4, -1.9] | 0.0072
Absolute Change in Liver Volume (MN) | 0.0 | -0.1 | -0.1 [-0.2, 0.0] | NA
Percentage Change in Platelet Count (%) | -9.1 | 32.0 | 41.1 [24.0, 58.2] | <0.0001
Absolute Change in Platelet Count (× 10^9/L) | -7.2 | 24.1 | 31.3 [18.8, 43.8] | NA
MN = Multiples of Normal, CI = confidence interval, NA = Not applicable

In the open-label extension phase of Trial 1 in naive GD1 patients, 38 of 40 patients who continued treatment with CERDELGA for 2 years demonstrated the following changes in clinical parameters from baseline to 2 years: mean (SD) percent change in spleen volume (MN) -51.1% (10.7); mean (SD) percent change in liver volume (MN) -16.1% (11.3); mean (SD) absolute change in hemoglobin level (g/dL) 1.3 (1.2), and mean (SD) percent change in platelet count (mm^3) 65.3% (40.9).

In a separate uncontrolled study (NCT00358150) of treatment-naive GD1 patients, improvements in spleen and liver volume, hemoglobin level, and platelet count continued through the 4-year treatment period.

14.2 Patients Switching from Enzyme Replacement Therapy to CERDELGA – Trial 2

Trial 2 (NCT00943111) was a randomized, open-label, active-controlled, non- inferiority, multicenter clinical study evaluating the efficacy and safety of CERDELGA compared with imiglucerase in 159 treated GD1 patients (median age 37.4 years) previously treated with enzyme replacement therapy (≥3 years of enzyme replacement therapy, dosed at 30–130 U/kg/month in at least 6 of the prior 9 months) who met pre-specified therapeutic goals at baseline. Pre-specified baseline therapeutic goals included: no bone crisis and free of symptomatic bone disease within the last year; mean hemoglobin level of ≥11 g/dL in females and ≥12 g/dL in males; mean platelet count ≥100,000/mm^3; spleen volume <10 times normal and liver volume <1.5 times normal.

Patients were randomized 2:1 to receive CERDELGA or imiglucerase for the duration of the 12-month primary analysis period. Seventy-five percent of patients randomized to CERDELGA were previously treated with imiglucerase; 21% with velaglucerase alfa and 4% were unreported. Patients randomized to CERDELGA treatment received a starting dose of 42 mg twice daily, with dose increases to 84 mg twice daily and 127 mg twice daily possible at Weeks 4 and 8 based on plasma trough concentrations of CERDELGA at Weeks 2 and 6, respectively. The percentage of patients receiving the 3 possible CERDELGA doses was: 42 mg twice daily (20%), 84 mg twice daily (32%) and 127 mg twice daily (48%). The CERDELGA treatment group was comprised of PM (4%), IM (10%), EM (80%) and URM (4%) patients.

At baseline, mean spleen volumes were 2.6 and 3.2 MN in the imiglucerase and CERDELGA groups, respectively, and liver volumes were 0.9 MN in both groups. Mean hemoglobin levels were 13.8 and 13.6 g/dL, and platelet counts were 192 and 207 × 10^9/L, respectively.

The primary composite endpoint required stability in all four component domains (hemoglobin level, platelet count, liver volume, and spleen volume) based on changes between baseline and 12 months. Stability was defined by the following pre-specified thresholds of change: hemoglobin level <1.5 g/dL decrease, platelet count <25% decrease, liver volume <20% increase and spleen volume <25% increase. The percentages of patients meeting the criteria for stability in the individual components of the composite endpoint were assessed as secondary efficacy endpoints.

CERDELGA met the criteria to be declared non-inferior to imiglucerase in maintaining patient stability. After 12 months of treatment, the percentage of patients meeting the primary composite endpoint was 84.8% for the CERDELGA group compared to 93.6% for the imiglucerase group. The lower bound of the 95% CI of the 8.8% difference, -17.6%, was within the pre-specified non-inferiority margin of -25%. At Month 12, the percentages of CERDELGA and imiglucerase patients respectively, who met stability criteria for the individual components of the composite endpoint were: hemoglobin level, 94.9% and 100%; platelet count, 92.9% and 100%; spleen volume, 95.8% and 100%; and liver volume, 96.0% and 93.6%. Of the patients who did not meet stability criteria for the individual components, 12 of 15 CERDELGA patients and 3 of 3 imiglucerase patients remained within therapeutic goals for GD1.

Mean changes from baseline in the hematological and visceral parameters through 12 months of treatment are shown in Table 11. There were no clinically meaningful differences between groups for any of the four parameters.

Table 11: Mean Changes from Baseline to Month 12 in Patients with GD1 Switching to CERDELGA in Trial 2
 | Imiglucerase (N=47) Mean [95% CI] | CERDELGA (N=99) Mean [95% CI]
Percentage Change in Spleen Volume MN (%) [Excludes patients with a total splenectomy.] | -3.0 [-6.4, 0.4] | -6.2 [-9.5, -2.8]
Absolute Change in Spleen Volume (MN) | -0.1 [-0.2, 0.0] | -0.2 [-0.3, -0.1]
Absolute Change in Hemoglobin Level (g/dL) | 0.0 [-0.2, 0.2] | -0.2 [-0.4, -0.1]
Percentage Change in Liver Volume MN (%) | 3.6 [0.6, 6.6] | 1.8 [-0.2, 3.7]
Absolute Change in Liver Volume (MN) | 0.0 [0.0, 0.1] | 0.0 [0.0, 0.0]
Percentage Change in Platelet Count (%) | 2.9 [-0.6, 6.4] | 3.8 [0.0, 7.6]
Absolute Change in Platelet Count (× 10^9/L) | 6.0 [-0.9, 13.0] | 9.5 [1.4, 17.6]
Patients Stable for 52 Weeks, n (%) (Composite Primary Endpoint) | 44 (93.6) | 84 (84.8)
MN = Multiples of Normal, CI = confidence interval

In the open-label extension phase of Trial 2, 141 of 146 patients (42 patients previously treated with enzyme treatment therapy and 99 who continued treatment with CERDELGA) were evaluated for stability, as defined in the initial 12 months of the trial, in clinical parameters (composite of spleen and liver volume, hemoglobin level, and platelet count). Stability was shown in 120/141 (85%) patients at one year and 111/129 (86%) patients at 2 years of CERDELGA exposure.

16 HOW SUPPLIED/STORAGE AND HANDLING

CERDELGA is supplied as 84 mg eliglustat in a capsule with a pearl blue-green opaque cap and pearl white opaque body imprinted with "GZ02" in black.

CERDELGA 84 mg capsules are supplied as:

NDC 58468-0220-1 – Carton containing 4 packs of capsules (56 capsules total). Each pack is composed of 1 blister card of 14 capsules and a cardboard wallet.

NDC 58468-0220-2 – Carton containing 1 pack of capsules (14 capsules total). Each pack is comprised of 1 blister card of 14 capsules and a cardboard wallet.

STORAGE AND HANDLING

Store at 68°F–77°F (20°C–25°C) with excursions permitted between 59°F and 86°F (15°C to 30°C) [see USP Controlled Room Temperature].

17 PATIENT COUNSELING INFORMATION

Advise the patient to read the FDA-approved patient labeling (Medication Guide).

Drug Interactions

Advise patients to discuss all the medications they are taking, including any herbal supplements or vitamins with their healthcare provider [see Contraindications (4), Warnings and Precautions (5), Drug Interactions (7)].

ECG Changes and Potential for Cardiac Arrhythmias

Advise patients to inform their healthcare provider of the following: history of congestive heart failure; recent acute myocardial infarction; bradycardia; heart block; ventricular arrhythmia; and long QT syndrome [see Warnings and Precautions (5.1)].

Advise patients to inform their healthcare provider if they develop new symptoms such as palpitations, fainting, and dizziness.

Administration Instructions

[See Dosage and Administration (2.4).]

Advise patients:

- Swallow capsules whole, preferably with water, and do not crush, dissolve, or open the capsules.
- CERDELGA can be taken with or without food.
- If a dose of CERDELGA is missed, take the prescribed dose at the next scheduled time; do not double the next dose.
- Avoid consumption of grapefruit or its juice.
- For patients currently treated with imiglucerase, velaglucerase alfa, or taliglucerase alfa, CERDELGA may be administered 24 hours after the last dose of the previous enzyme replacement therapy (ERT).

Genzyme Corporation
450 Water Street
Cambridge, MA 02141
A SANOFI COMPANY

For patent information: https://www.sanofi.us/en/products-and-resources/patents

CERDELGA is a registered trademark of Genzyme Corporation.

MEDICATION GUIDE
CERDELGA® (sir-DEL-guh)
(eliglustat) capsules

What is the most important information I should know about CERDELGA?
CERDELGA can affect the way other medicines work and other medicines can affect how CERDELGA works. Using CERDELGA with other medicines or herbal supplements may cause an increased risk of side effects.
Especially tell your doctor if you take:

- St. John's Wort (Hypericum perforatum)
- Medicine for:
  - Fungal infections
  - Tuberculosis
  - Seizures
  - Heart conditions or high blood pressure
  - Depression or other mental health problems

If you take any medicines for the conditions listed above, your doctor may need to prescribe a different medicine, change your dose of other medicines, or change your dose of CERDELGA. Tell your doctor about any new medicines before you start taking them.

What is CERDELGA?
CERDELGA is a prescription medicine used for the long-term treatment of Gaucher disease type 1 (GD1) in adults.
CERDELGA is not used in certain people with Gaucher disease type 1. Your doctor will perform a test to make sure that CERDELGA is right for you.
It is not known if CERDELGA is safe and effective in children.

What should I tell my doctor before taking CERDELGA?
Before taking CERDELGA, tell your doctor about all of your medical conditions, including if you:

- have heart problems, including a condition called long QT syndrome
- have a history of a heart attack
- have kidney or liver problems
- are pregnant or planning to become pregnant. It is not known if CERDELGA will harm your unborn baby.
- are breastfeeding or planning to breastfeed. It is not known if CERDELGA passes into your breast milk. You and your doctor will decide if you should take CERDELGA or breastfeed. You should not do both.

Tell your doctor about all of the medicines you take, including prescription and over-the-counter medicines, vitamins, and herbal supplements. See "What is the most important information I should know about CERDELGA?"

How should I take CERDELGA?

- Take CERDELGA exactly as your doctor tells you to take it.
- Your doctor may change your dose if needed.
- Take CERDELGA capsules whole, preferably with water. Do not open, crush, or dissolve capsules before swallowing.
- CERDELGA can be taken with or without food.
- If you miss a dose of CERDELGA, take the next dose at the usual time. Do not take two doses of CERDELGA at the same time.
- If you take too much CERDELGA, call your doctor or go to the nearest hospital emergency room right away.

What should I avoid while taking CERDELGA?
Avoid eating or drinking grapefruit products while taking CERDELGA. Grapefruit products can increase the amount of CERDELGA in your body.

What are the possible side effects of CERDELGA?
See "What is the most important information I should know about CERDELGA?"

- CERDELGA, used with certain other medicines, may cause changes in the electrical activity of your heart (ECG changes) and irregular heart beat (arrhythmias). Tell your doctor if you have new symptoms such as palpitations, fainting, or dizziness.

The most common side effects of CERDELGA include: tiredness, headache, nausea, diarrhea, and pain in the arms, legs, back, or stomach (abdomen).
Tell your doctor if you have any side effect that bothers you or that does not go away. These are not all the possible side effects of CERDELGA.
Call your doctor for medical advice about side effects. You may report side effects to FDA at 1-800-FDA-1088.

How should I store CERDELGA?

- Store CERDELGA at room temperature between 68°F-77 °F (20°C-25 °C).
- Keep CERDELGA and all medicines out of reach of children.

General information about the safe and effective use of CERDELGA.
Medicines are sometimes prescribed for purposes other than those listed in a Medication Guide. Do not use CERDELGA for a condition for which it was not prescribed. Do not give CERDELGA to other people, even if they have the same symptoms you have. It may harm them.
If you would like more information, talk with your doctor. You can ask your doctor or pharmacist for information about CERDELGA that is written for health professionals.
For more information, go to www.cerdelga.com or call 1-800-745-4447.

What are the ingredients in CERDELGA?
Active ingredient: eliglustat
Inactive ingredients: microcrystalline cellulose, lactose monohydrate, hypromellose, glyceryl behenate, gelatin, candurin silver fine, yellow iron oxide, and FD&C blue 2.
Genzyme Corporation, 450 Water Street, Cambridge, MA 02141 A SANOFI COMPANY
CERDELGA is a registered trademark of Genzyme Corporation. ©2024 Genzyme Corporation. All rights reserved.

This Medication Guide has been approved by the U.S. Food and Drug Administration.

Issued: January 2024

PRINCIPAL DISPLAY PANEL - 4 Blister Pack Carton

NDC 58468-0220-1

Cerdelga®
(eliglustat) capsules

84 mg*

*Each capsule contains 84 mg of eliglustat which is
equivalent to 100 mg of eliglustat tartrate

Dispense the enclosed Medication Guide to each patient

Four cartons of 14 capsules each

Rx Only